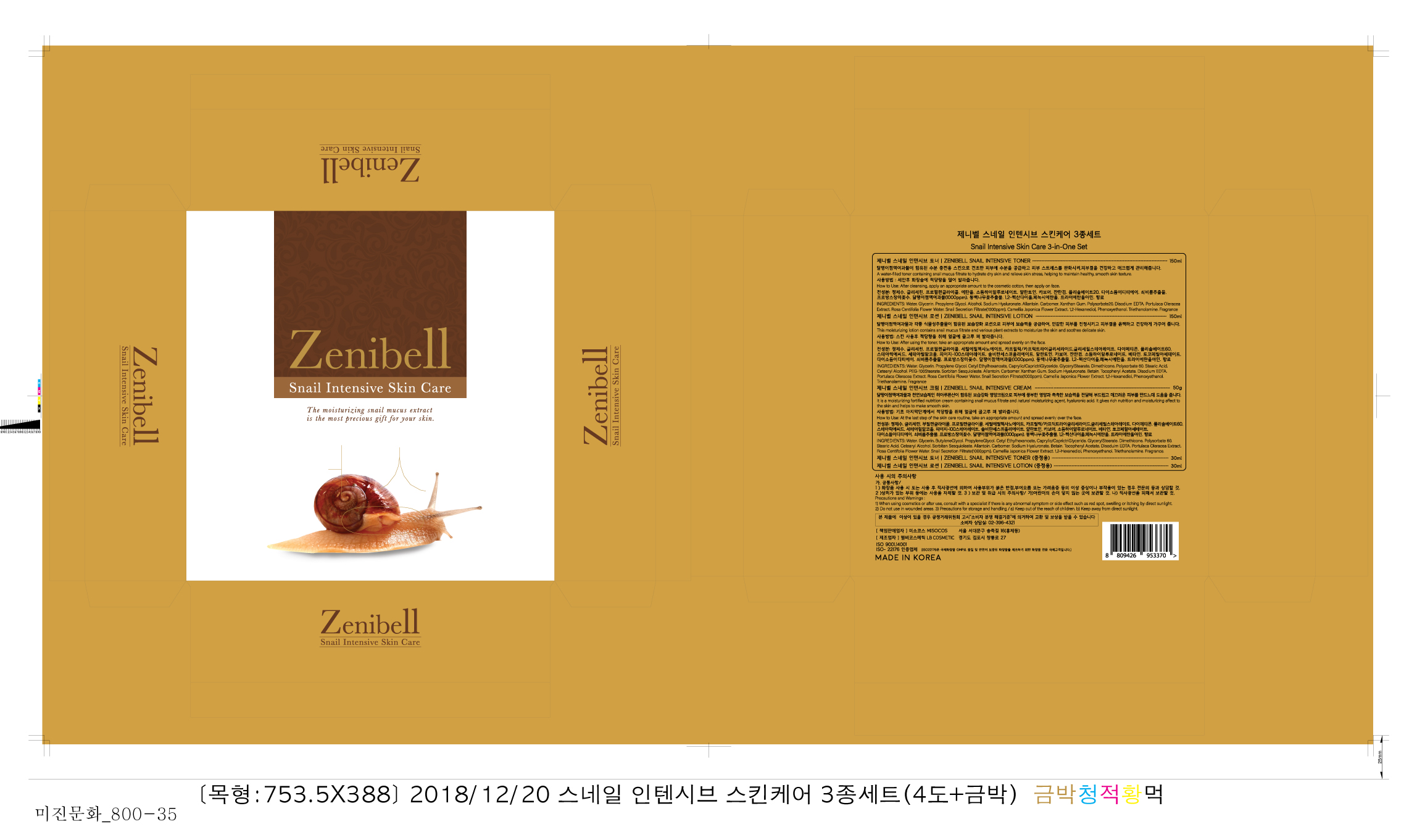 DRUG LABEL: Zenibell Snail IntensiveCream
NDC: 73466-0002 | Form: CREAM
Manufacturer: MISOCOS
Category: otc | Type: HUMAN OTC DRUG LABEL
Date: 20240705

ACTIVE INGREDIENTS: GLYCERIN 2 g/100 g
INACTIVE INGREDIENTS: WATER; STEARIC ACID

Drug Facts

ACTIVE INGREDIENT

glycerin

INACTIVE INGREDIENT

propylene glycol, steaqric acid, etc

PURPOSE

for skin protectant

keep out of reach of the children

INDICATIONS AND USAGE

take a suitable amount on the skin

WARNINGS

■ if following abnormal symptoms occurs after use , stop use and consult with a skin specialist

red specks, swelling, itching

■ don’t use on the part where there is injury, eczema, or dermatitis

Keep out of reach of children

■ if swallowed, get medical help or contact a person control center immediately

DOSAGE AND ADMINISTRATION

for external use only